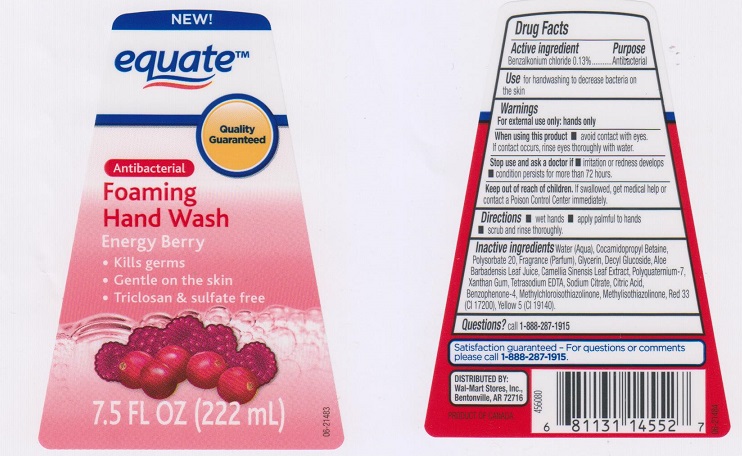 DRUG LABEL: Equate Foaming Hand Wash
NDC: 49035-036 | Form: SOAP
Manufacturer: Wal-mart Stores Inc
Category: otc | Type: HUMAN OTC DRUG LABEL
Date: 20160822

ACTIVE INGREDIENTS: BENZALKONIUM CHLORIDE 1.3 mg/1 mL
INACTIVE INGREDIENTS: WATER; COCAMIDOPROPYL BETAINE; POLYSORBATE 20; GLYCERIN; DECYL GLUCOSIDE; ALOE VERA LEAF; GREEN TEA LEAF; POLYQUATERNIUM-7 (70/30 ACRYLAMIDE/DADMAC; 1600000 MW); XANTHAN GUM; EDETATE SODIUM; SODIUM CITRATE; CITRIC ACID MONOHYDRATE; SULISOBENZONE; METHYLCHLOROISOTHIAZOLINONE; METHYLISOTHIAZOLINONE; D&C RED NO. 33; FD&C YELLOW NO. 5

DRUG FACTS

Active ingredient

Benzalkonium chloride 0.13%

Purpose

Antibacterial

Use

for handwashing to decrease bacteria on the skin.

Warnings

For external use only: hands only

When using this product

- avoid contact with eyes. If contact occurs, rinse eyes thoroughly with water.

Stop use and ask a doctor if

- irritation or redness develops.
- condition persists for more than 72 hours.

Keep out of reach of children.

If swallowed, get medical help or contact a Poison Control Center immediately.

Directions

- wet hands
- apply palmful to hands
- scrub and rinse thoroughly

Inactive ingredients

Water (Aqua), Cocamidopropyl Betaine, Polysorbate 20, Fragrance (Parfum), Glycerin, Decyl Glucoside, Aloe Barbadensis Leaf Juice, Camellia Sinensis Leaf Extact, Polyquaternium-7, Xanthan Gum, Tetrasodium EDTA, Sodium Citrate, Citric Acid, Benzophenone-4, Methylchloroisothiazolinone, Methylisothiazolinone, Red 33 (CI 17200), Yellow 5 (CI 19140).

Questions?

Call 1-888-287-1915